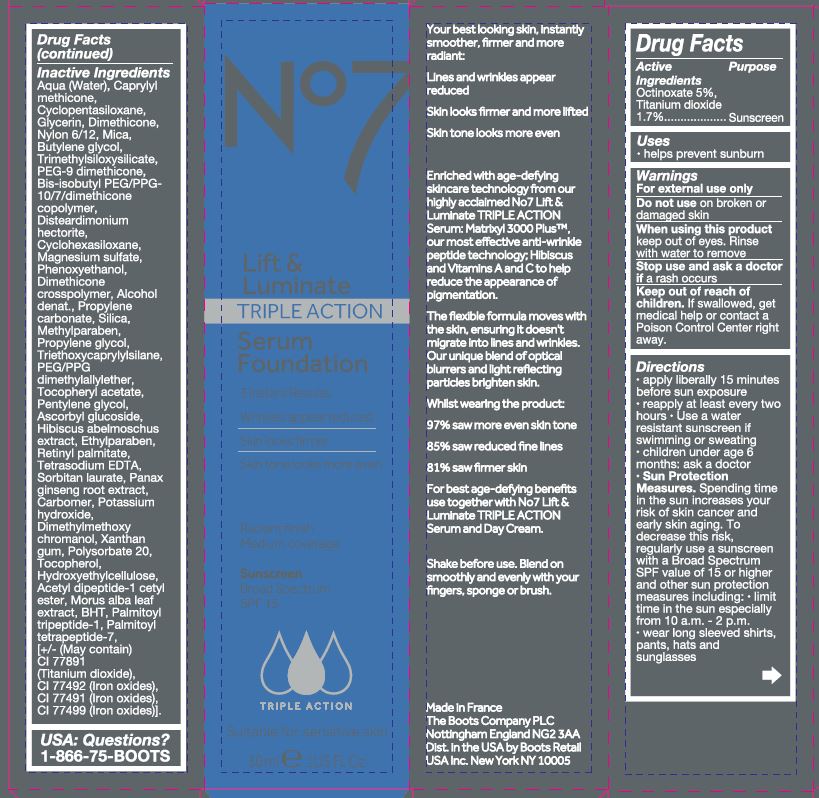 DRUG LABEL: No7 Lift and Luminate Triple Action Serum Foundation Sunscreen Broad Spectrum SPF 15 Warm Beige
NDC: 61589-9554 | Form: CREAM
Manufacturer: BCM Cosmetique SAS
Category: otc | Type: HUMAN OTC DRUG LABEL
Date: 20251022

ACTIVE INGREDIENTS: OCTINOXATE 1.5 g/30 g; TITANIUM DIOXIDE 0.51 g/30 g
INACTIVE INGREDIENTS: WATER; CYCLOMETHICONE 5; NYLON 612 (MW 14000); GLYCERIN; MICA; DIMETHICONE; BUTYLENE GLYCOL; PEG-9 DIMETHICONE; CYCLOMETHICONE 6; TRIMETHYLSILOXYSILICATE (M/Q 0.6-0.8); DISTEARDIMONIUM HECTORITE; MAGNESIUM SULFATE, UNSPECIFIED; PHENOXYETHANOL; .ALPHA.-TOCOPHEROL ACETATE; PROPYLENE GLYCOL; METHYLPARABEN; PROPYLENE CARBONATE; ETHYLPARABEN; TRIETHOXYCAPRYLYLSILANE; PENTYLENE GLYCOL; ASCORBYL GLUCOSIDE; PANAX GINSENG ROOT WATER; CARBOMER 940; DIMETHYLMETHOXY CHROMANOL; POTASSIUM HYDROXIDE; POLYSORBATE 20; XANTHAN GUM; TOCOPHEROL; N-ACETYL DIPEPTIDE-1; VITAMIN A PALMITATE; MORUS ALBA LEAF; ETIDRONATE TETRASODIUM; PALMITOYL TRIPEPTIDE-1; PALMITOYL TETRAPEPTIDE-7; FERRIC OXIDE YELLOW; FERRIC OXIDE RED; FERROSOFERRIC OXIDE

No7 Lift and Luminate Triple Action Serum Foundation Sunscreen Broad Spectrum SPF 15 Warm Beige

Carton Active Ingredients Section

Active Ingredients

Octinoxate 5% Titanium dioxide 1.7%

Uses

Uses - helps prevent sunburn

Warnings

For external use only

Do not use on damaged or broken skin

When using this product keep out of eyes. Rinse with water to remove

Warnings

For external use only

Do not use on damaged or broken skin

When using this product keep out of eyes. Rinse with water to remove

Ask a doctor

Stop use and ask a doctor if rash occurs.

Keep out of reach of children. If swallowed, get medical help or contact a Poison Control Center right away.

Directions

Directions for suncreen use

apply liberally 15 minutes before sun exposure

reapply at least every 2 hours

use a water resistant sunscreen if swimming or sweating

children under 6 months of age: Ask a doctor

Sun Protection Measures. Spending time in the sun increases your risk of skin cancer and early skin aging. To decrease this risk, regularly use a sunscreen with a Broad Spectrum SPF value of 15 or higher and other sun protection measures including:

limit time in the sun, especially from 10 a.m. - 2 p.m.

wear long-sleeved shirts, pants, hats, and sunglasses

Directions

Directions for suncreen use

apply liberally 15 minutes before sun exposure

reapply at least every 2 hours

use a water resistant sunscreen if swimming or sweating

children under 6 months of age: Ask a doctor

Sun Protection Measures. Spending time in the sun increases your risk of skin cancer and early skin aging. To decrease this risk, regularly use a sunscreen with a Broad Spectrum SPF value of 15 or higher and other sun protection measures including:

limit time in the sun, especially from 10 a.m. - 2 p.m.

wear long-sleeved shirts, pants, hats, and sunglasses

Other information

Protect the product in this container from excessive heat and direct sun

Inactive ingredients

Aqua (Water), Caprylyl methicone, Cyclopentasiloxane, Glycerin, Dimethicone, Nylon 6/12, Mica, Butylene glycol, Trimethylsiloxysilicate, PEG-9 dimethicone, Bis-isobutyl PEG/PPG-10/7 dimethicone copolymer, Disteardimonium hectorite, Cyclohexasiloxane, Magnesium sulfate, Phenoxyethanol, Dimethicone crosspolymer, Alcohol denat., Propylene carbonate, Silica, Methylparaben, Propylene glycol, Triethoxycaprylysilane, PEG-PPG dimethylallylether, Tocopheryl acetate, Pentylene glycol, Ascorbyl glucoside, Hibiscus abelmoschus extract, Ethylparaben, Retinyl palmitate, Tetrasodium EDTA, Sorbitan laurate, Panax ginseng root extract, Carbomer, Potassium hydroxide, Dimethylmethoxychromanol, Xanthan gum, Polysorbate 20, Tocopherol, Hydroxyethylcellulose, Acetyl dipeptide-1 cetyl ester, Morus alba leaf extract, BHT, Palmitoyl tripeptide--1, Palmitoyl tetrapeptide-7, [+/- (May contain) CI 77891 (Titanium dioxide), CI 77492 (Iron oxides), CI 77491 (Iron oxides), CI 77499 (Iron oxides)].

Description

Your best looking skin, instantly smoother, firmer and more radiant:

Lines and wrinkles appear reduced

Skin looks firmer and more lifted

Skin tone looks more even

Enriched with age-defying skincare technology from our highly acclaimed No7 Lift And Luminate TRIPLE ACTION Serum:Matrixyl 3000 PlusTMour most effective anti-wrinkle peptide technology:Hibiscus and Vitamins A and C to help reduce the appearance of pigmentation.

The flexible formula moves with the skin, ensuring it doesn't muigrate into lines and wrinkles. Our uhique blend of optical blurrers and light reflecting particles brighten the skin.

Whilst wearing the product:

97% saw more even skin tone

85% saw reduced fine lines

81% saw firmer skin

For best age-defying benefts use together with No7 Lift and Luminate TRIPLE ACTION Serum and Day Cream

Shake before use. Blend on smoothly and evenly with your fingers, sponge or brush.

Information

Made in France

The Boots Company PLC

Nottingham England NG2 3AA

Dist. in the USA by Boots Retail USA Inc.

New York NY 10005

Warnings

Warning: Avoid contact with eyes. If product gets into the eyes, rinse well with water immediately.

Description

No7 Lift & Luminate Triple Action Serum Foundation Sunscreen Broad Spectrum SPF 15

3 Instant Results

Wrinkles appear reduced

Skin looks firmer

Skin tone looks more even

Radiant finish

Medium coverage

Suitable for sensitive skin

30 ml e 1 US Fl.Oz.